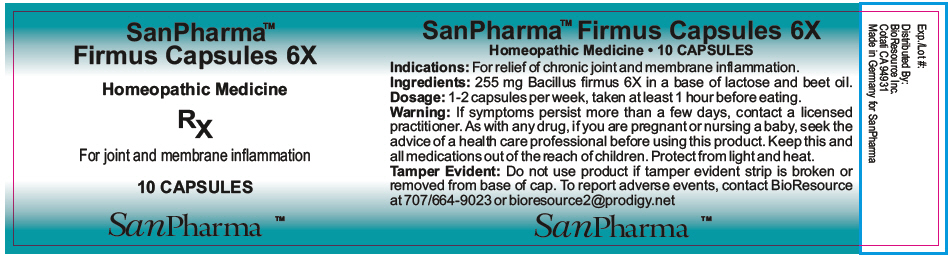 DRUG LABEL: Firmus
NDC: 54256-008 | Form: CAPSULE
Manufacturer: BioResource Inc.
Category: homeopathic | Type: HUMAN OTC DRUG LABEL
Date: 20151102

ACTIVE INGREDIENTS: Bacillus firmus 6 [hp_X]/1 1
INACTIVE INGREDIENTS: Lactose; Beet

Firmus capsules

Indications

PURPOSE

For relief of chronic joint and membrane inflammation.

Ingredients

INACTIVE INGREDIENT

255 mg Bacillus firmus 6X in a base of lactose and beet oil.

Dosage

1-2 capsules per week, taken at least 1 hour before eating.

Warning

If symptoms persist more than a few days, contact a licensed practitioner. As with any drug, if you are pregnant or nursing a baby, seek the advice of a health care professional before using this product.

KEEP OUT OF REACH OF CHILDREN

Keep this and all medications out of the reach of children. Protect from light and heat.

Tamper Evident

Do not use product if tamper evident strip is broken or removed from base of cap. To report adverse events, contact BioResource at 707/664-9023 or bioresource2@prodigy.net

Distributed By:
BioResource Inc.
Cotati CA 94931

PRINCIPAL DISPLAY PANEL - 10 Capsule Bottle Label

SanPharma™
Firmus Capsules 6X

Homeopathic Medicine

RX

For joint and membrane inflammation

10 CAPSULES

SanPharma ™